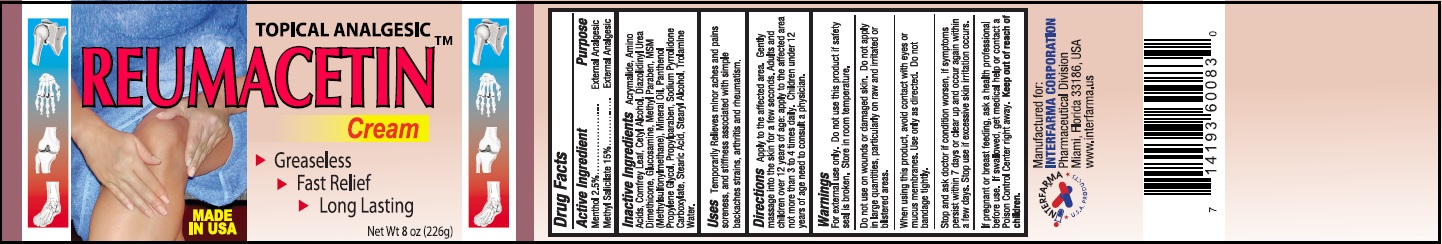 DRUG LABEL: FAST RELIEF REUMACETIN
NDC: 69706-0204 | Form: CREAM
Manufacturer: Interfarma Corp
Category: otc | Type: HUMAN OTC DRUG LABEL
Date: 20151001

ACTIVE INGREDIENTS: MENTHOL 2.5 g/100 g; METHYL SALICYLATE 15 g/100 g
INACTIVE INGREDIENTS: ACRYLAMIDE; AMINO ACIDS, WHEAT; CETYL ALCOHOL; COMFREY LEAF; DIAZOLIDINYL UREA; DIMETHICONE; DIMETHYL SULFONE; GLUCOSAMINE; METHYLPARABEN; MINERAL OIL; PANTHENOL; PROPYLENE GLYCOL; PROPYLPARABEN; SODIUM PYRROLIDONE CARBOXYLATE; STEARIC ACID; STEARYL ALCOHOL; TROLAMINE; WATER

FAST RELIEF REUMACETIN

DRUG FACTS

Active Ingredient: Purpose:

Menthol 2.5%...................................External Analgesic

Methyl Salicylate 15%......................External Analgesic

Uses

Temporarily relieves minor aches and pains of muscles and joints associated with simple backache, arthritis, strains, bruises, sprains.

Warnings:

- For external use only.
- Do not use this product if safety seal is broken. Store in room temperature.
- Do not use on wounds or damaged skin. Do not apply in large quantities, particularly on raw and irritated or blistered areas.
- When using this product, avoid contact with eyes or mucus membranes. Use only as directed. Do not bandage tightly.
- Stop and ask doctor if condition worsen, if symptoms persist within 7 days or clear up and occur again within a few days. Stop use if excessive skin irritation occurs.
- If pregnant or breast feeding, ask a health professional before use. If swallowed, get medical help or contact a Poison Control Center right away.

Keep out of reach of children to avoid accidental poisoning.

DOSAGE AND ADMINISTRATION

Caution: Discontinue use if excessive irritation of the skin develops. Avoid getting into eyes or mucous membranes. If condition worsens, or symptoms persist for more than 7 days or clear up and occur again within a few days, or redness is present, or in conditions affecting children under 12 years of age, discontinue use and consult a physician immediately.

Directions

Apply to the affected area. Gently massage into the skin for a few seconds. Adults and children over 12 years of age: apply to the affected area not more than 3 to 4 times daily. Children under 12 years of age need to consult a physician.

Inactive Ingredients:

Acrymalide, Amino Acids, Comfrey Leaf, Cetyl Alcohol, Diazolidinyl Urea, Dimethicone, Glucosamine, Methyl Paraben, MSM (Methylsulfonylmethane), Mineral Oil, Panthenol, Propylene Glycol, Propylparaben, Sodium Pyrrolidone Carboxylate, Stearic Acid, Stearyl Alcohol, Trolamine, Water.

Manufactured for:

Interfarma Corp.

Miami, FL 33186.

FAST RELIEF REUMACETIN

For Temporarily Relieves minor aches and pains soreness, and stiffness associated with simple backaches strains, arthritis and rheumatism.

Net Wt 8 oz (226g)

Made in USA